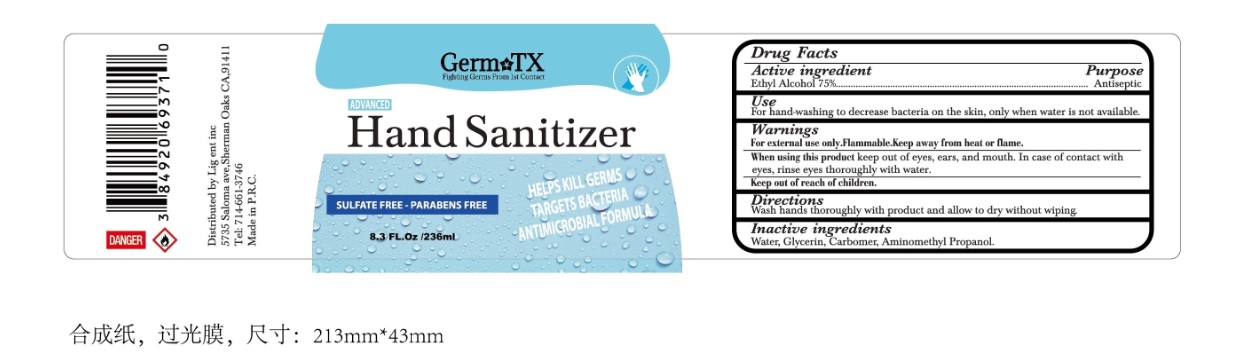 DRUG LABEL: Germ TX Hand Sanitizer
NDC: 77247-205 | Form: GEL
Manufacturer: Lig Ent. Inc.
Category: otc | Type: HUMAN OTC DRUG LABEL
Date: 20200506

ACTIVE INGREDIENTS: ALCOHOL 75 mL/100 mL
INACTIVE INGREDIENTS: WATER; GLYCERIN; CARBOMER HOMOPOLYMER, UNSPECIFIED TYPE; AMINOMETHYLPROPANOL

GERM TX Hand Sanitizer

Active ingredient

Ethyl Alcohol 75%

Purpose

Antiseptic

Use

For hand-washing to decrease bacteria on the skin, only when water is not available.

Warnings

For external use only. Flammable. Keep away from heat or flame.

When using this product keep out of eyes, ears, and mouth. In case of contact with eyes, rinse eyes thoroughly with water.

Keep out of reach of children.

Directions

Wash hands thoroughly with product and allow to dry without wiping.

Inactive ingredients

Water, Glycerin, Carbomer, Aminomethyl Propanol.

Fighting Germs From 1st Contact

ADVANCED

SULFATE FREE - PARABENS FREE

HELPS KILL GERMS

TARGETS BACTERIA

ANTIMICROBIAL FORMULA

Distributed by Lig ent inc

5735 Saloma ave,Sherman Oaks CA,91411

Tel: 714-661-3746

Made in P.R.C.

DANGER